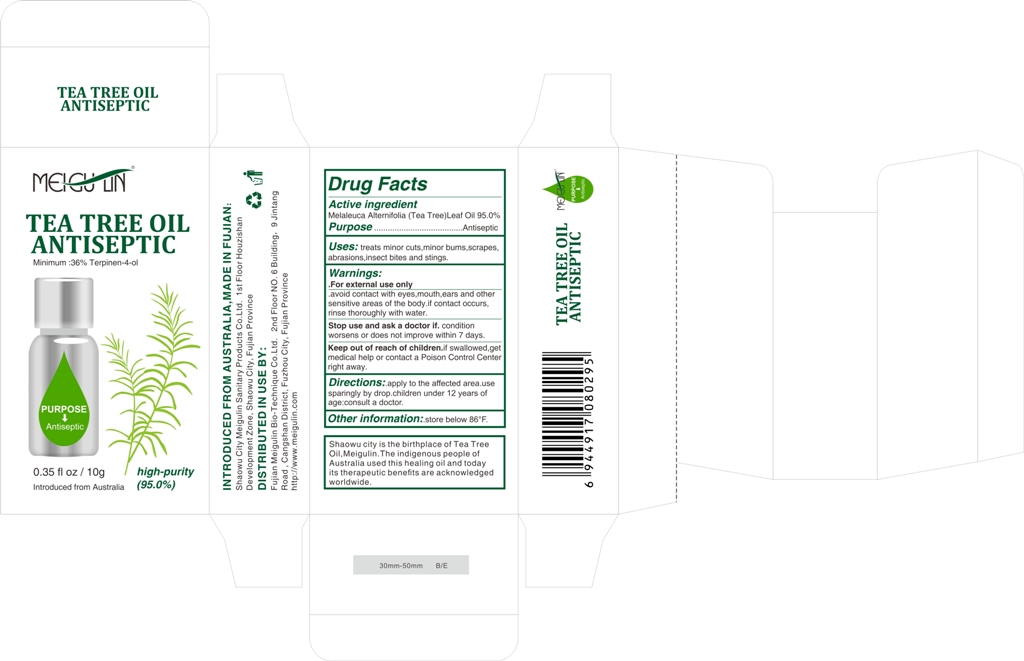 DRUG LABEL: Tea Tree Oil
NDC: 70876-002 | Form: LIQUID
Manufacturer: Fujian Meigulin Bio-Technique Co., Ltd.
Category: otc | Type: HUMAN OTC DRUG LABEL
Date: 20200117

ACTIVE INGREDIENTS: MELALEUCA ALTERNIFOLIA LEAF 0.95 g/1 g
INACTIVE INGREDIENTS: WATER

70876-002

Active ingredient

MELALEUCA ALTERNIFOLIA LEAF 100%

Purpose

Antiseptic

Uses

treats minor cuts,minor bums,scrapes,abrasions,insect bites and stings

Warnings

For External use only.
avoid contact wih eyes,mouth,ears and other sensitive areas of the body.if contact occurs,rinse thoroughly with water.

stop use and ask a doctor if condition worsens or does not improve within 7 days.

keep out of reach of children .if seallowed ,get medical help or contact a Poison Control Center right away.

Directions

apply to the affected area,use sparingly by drop,children under 12 years of age :consult a doctor.